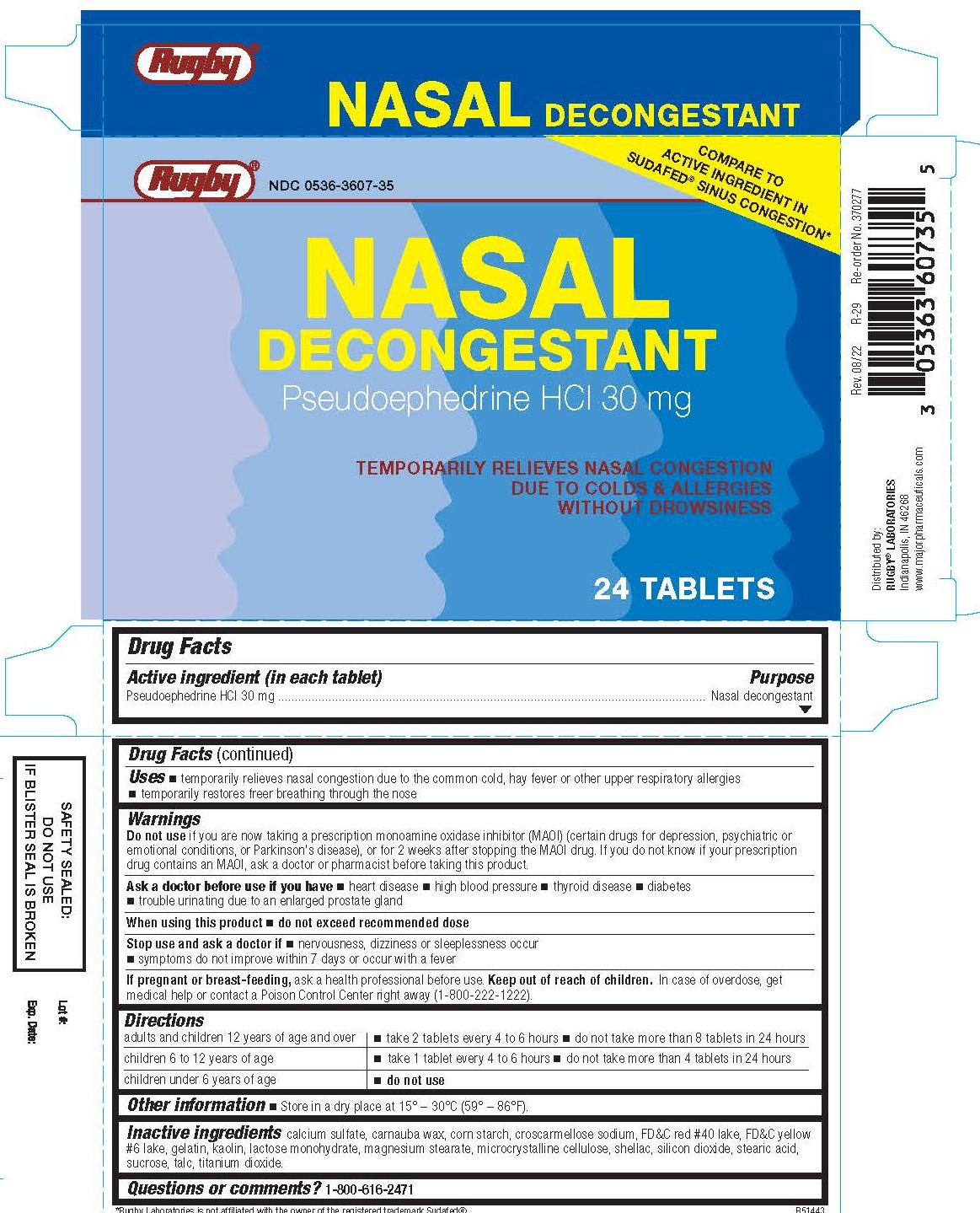 DRUG LABEL: Nasal Decongestant
NDC: 0536-3607 | Form: TABLET
Manufacturer: Rugby Laboratories
Category: otc | Type: HUMAN OTC DRUG LABEL
Date: 20240111

ACTIVE INGREDIENTS: PSEUDOEPHEDRINE HYDROCHLORIDE 30 mg/1 1
INACTIVE INGREDIENTS: CROSCARMELLOSE SODIUM; FD&C YELLOW NO. 6; MAGNESIUM STEARATE; CELLULOSE, MICROCRYSTALLINE; TITANIUM DIOXIDE; CALCIUM SULFATE ANHYDROUS; CARNAUBA WAX; FD&C RED NO. 40; GELATIN; KAOLIN; LACTOSE MONOHYDRATE; TALC; SHELLAC; SILICON DIOXIDE; STEARIC ACID; SUCROSE; STARCH, CORN

1004 - Rugby

Drug Facts

Active ingredient (in each tablet)

Pseudoephedrine HCl 30 mg

Purpose

Nasal decongestant

Uses

- temporarily relieves nasal congestion due to the common cold, hay fever or other upper respiratory allergies
- temporarily restores freer breathing through the nose

Warnings

Do not use

- if you are now taking a prescription monoamine oxidase inhibitor (MAOI) (certain drugs for depression, psychiatric or emotional conditions, or Parkinson's disease), or 2 weeks after stopping the MAOI drug. If you do not know if your prescription drug contains and MAOI, ask a doctor or pharmacist before taking this product.

Ask a doctor before use if you have

- heart disease
- high blood pressure
- thyroid disease
- diabetes
- trouble urinating due to an enlarged prostate gland

When using this product

- do not exceed recommended dose

Stop use and ask a doctor if

- nervousness, dizziness, or sleeplessness occur
- symptoms do not improve within 7 days or occur with fever

If pregnant or breast-feeding,

ask a health professional before use.

Keep out of reach of children.

- In case of overdose, get medical help or contact a Poison Control Center right away (1-800-222-1222).

Directions

adults and children 12 years and older | take 2 tablets every 4 to 6 hours; do not take more than 8 tablets in 24 hours
children ages 6 to 12 years | take 1 tablet every 4 to 6 hours; do not take more than 4 tablets in 24 hours
children under 6 years | do not use

Other information

- Store in a dry place at 15° – 30°C (59° – 86°F).

Inactive ingredients

calcium sulfate, carnauba wax, corn starch, croscarmellose sodium, FD&C red #40 lake, FD&C yellow #6 lake, gelatin, kaolin, lactose monohydrate, magnesium stearate, microcrystalline cellulose, shellac, silicon dioxide, stearic acid, sucrose, talc, titanium dioxide.

Questions or comments?

1-800-616-2471

*Rugby Laboratories is not affiliated with the owner of the registered trademark Sudafed®

SAFETY SEALED: DO NOT USE IF BLISTER SEAL IS BROKEN

Distributed by:

RUGBY® LABORATORIES

Indianapolis, IN 46268

www.majorpharmaceuticals.com

Re-order No. 370277

Rev. 08/22 R-29

PACKAGE LABEL

Rugby®

Compare to active ingredient in Sudafed® Sinus Congestion*

NDC 0536-3607-35

Nasal Decongestant

Pseudoephedrine HCl 30 mg

Temporarily relieves nasal congestion due to colds & allergies without drowsiness

24 tablets